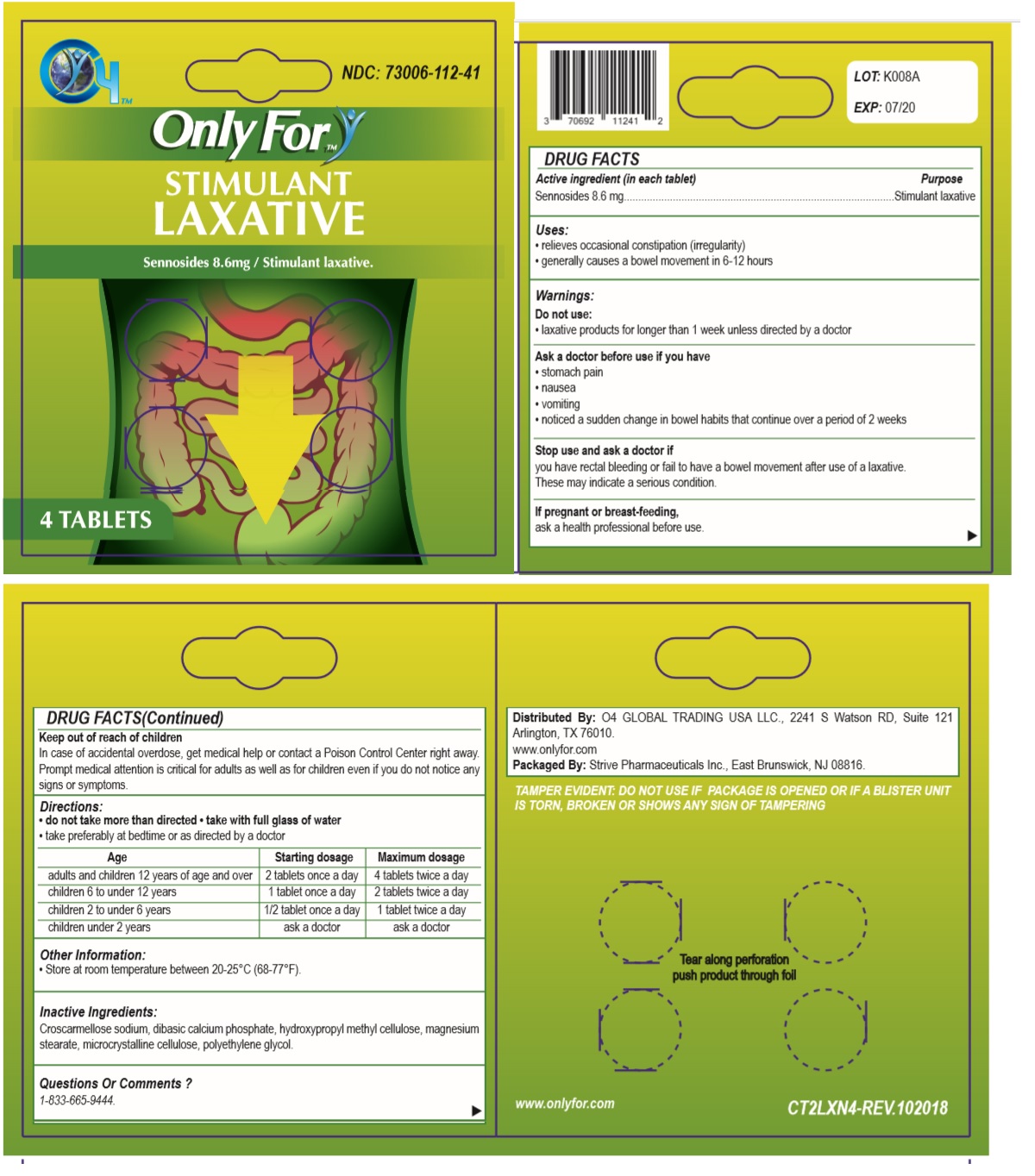 DRUG LABEL: Only For
NDC: 73006-112 | Form: TABLET
Manufacturer: O4 Global Trading Usa, Llc 
Category: otc | Type: HUMAN OTC DRUG LABEL
Date: 20190425

ACTIVE INGREDIENTS: SENNOSIDES 8.6 mg/1 1
INACTIVE INGREDIENTS: CROSCARMELLOSE SODIUM; DIBASIC CALCIUM PHOSPHATE DIHYDRATE; HYPROMELLOSE 2910 (5 MPA.S); MAGNESIUM PALMITOSTEARATE; MICROCRYSTALLINE CELLULOSE 101; POLYETHYLENE GLYCOL 400

Only For - STIMULANT LAXATIVE

Active ingredient (in each tablet)

Sennosides 8.6 mg

Purpose

Stimulant laxative

Uses:

• relieves occasional constipation (irregularity)

• generally causes a bowel movement in 6‐12 hours

Warnings:

Do not use:

• laxative products for longer than 1 week unless directed by a doctor

Ask a doctor before use if you have

• stomach pain

• nausea

• vomiting

• noticed a sudden change in bowel habits that continue over a period of 2 weeks

Stop use and ask a doctor if

you have rectal bleeding or fail to have a bowel movement after use of a laxative. These may indicate a serious condition.

If pregnant or breast-feeding,

ask a health professional before use.

Keep out of reach of children

In case of accidental overdose, get medical help or contact a Poison Control Center right away. Prompt medical attention is critical for adults as well as for children even if you do not notice any signs or symptoms.

Directions:

• do not take more than directed • take with full glass of water

• take preferably at bedtime or as directed by a doctor

Age | Starting dosage | Maximum dosage
adults and children 12 years of age and over | 2 tablets once a day | 4 tablets twice a day
children 6 to under 12 years | 1 tablet once a day | 2 tablets twice a day
children 2 to under 6 years | 1/2 tablet once a day | 1 tablet twice a day
children under 2 years | ask a doctor | ask a doctor

Other Information:

• Store at room temperature between 20-25°C (68-77°F).

Inactive Ingredients:

Croscarmellose sodium, dibasic calcium phosphate, hydroxypropyl methyl cellulose, magnesium stearate, microcrystalline cellulose, polyethylene glycol.

Questions Or Comments ?

1-833-665-9444.

Distributed By: O4 GLOBAL TRADING USA LLC., 2241 S Watson RD, Suite 121 Arlington, TX 76010.

www.onlyfor.com

Packaged By: Strive Pharmaceuticals Inc., East Brunswick, NJ 08816

TAMPER EVIDENT: DO NOT USE IF PACKAGE IS OPENED OR IF A BLISTER UNIT IS TORN, BROKEN OR SHOWS ANY SIGN OF TAMPERING

Tear along perforation push product through foil

CT2LXN4-REV.102018